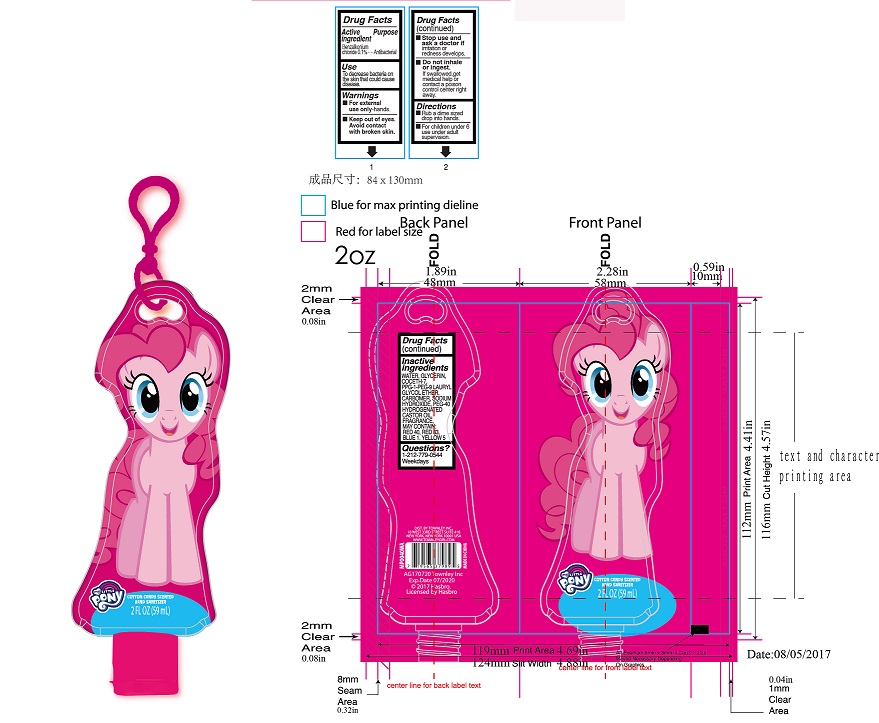 DRUG LABEL: My Little Pony Cotton Candy Scented
NDC: 58737-219 | Form: GEL
Manufacturer: Townley Inc.
Category: otc | Type: HUMAN OTC DRUG LABEL
Date: 20170822

ACTIVE INGREDIENTS: BENZALKONIUM CHLORIDE 0.1 g/100 g
INACTIVE INGREDIENTS: CARBOMER COPOLYMER TYPE A (ALLYL PENTAERYTHRITOL CROSSLINKED); POLYOXYL 40 HYDROGENATED CASTOR OIL; D&C RED NO. 33; FD&C RED NO. 40; WATER; GLYCERIN; COCETH-7; PPG-1-PEG-9 LAURYL GLYCOL ETHER; SODIUM HYDROXIDE; FD&C BLUE NO. 1; FD&C YELLOW NO. 5

Active Ingredient

Benzalkonium Chloride 0.1%

Purpose

Antibacterial

Use

To decrease bacteria on the skin that could cause disease

Directions

- Rub a dime sized drop into hands.
- For children under 6 use under adult supervision.

Warnings

- For external use only - hands.
- Keep out of eyes. Avoid contact with broken skin.
- Stop use and ask a doctor if irritation or redness develops.
- Do not inhale or ingest. If swallowed, get medical help or contact a poison control center right away.

keep out of reach of children

Inactive ingredients

water, glycerin, coceth-7, PPG-1-PEG-9 lauryl glycol ether, carbomer, sodium hydroxide, PEG-40 hydrogenated castor oil, fragrance, may contain: red 40, red 33, blue 1, yellow 5.